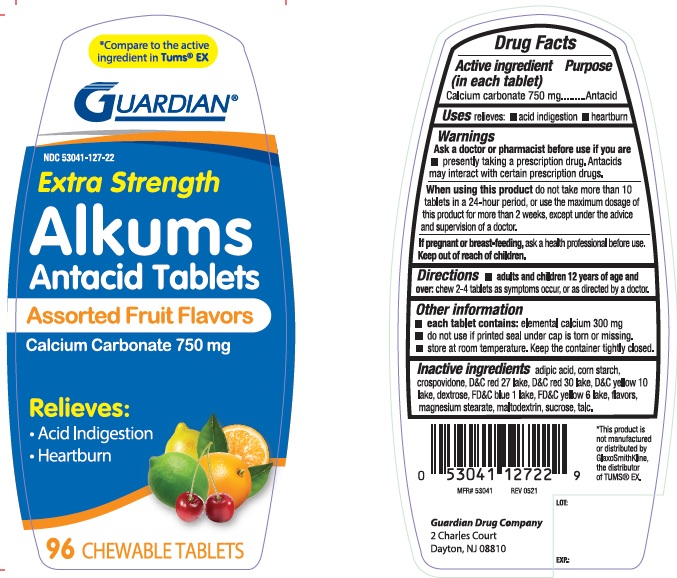 DRUG LABEL: Antacid
NDC: 53041-127 | Form: TABLET, CHEWABLE
Manufacturer: Guardian Drug Company
Category: otc | Type: HUMAN OTC DRUG LABEL
Date: 20220113

ACTIVE INGREDIENTS: CALCIUM CARBONATE 750 1/1 1
INACTIVE INGREDIENTS: ADIPIC ACID; STARCH, CORN; CROSPOVIDONE; D&C RED NO. 27; D&C RED NO. 30; D&C YELLOW NO. 10; DEXTROSE; FD&C BLUE NO. 1; FD&C YELLOW NO. 6; MAGNESIUM STEARATE; MALTODEXTRIN; SUCROSE; TALC

Alkums Antacid Tablets Assorted Fruit

Active ingredient (in each tablet)

Calcium carbonate 750mg

Purpose

Antacid

Uses

relieves:

acid indigestion

heartburn

Warnings

Ask a doctor or pharmacist before use if you are

taking a prescription drug. Antacids may interact with certain prescription drugs.

When using this product

do not take more than 10 tablets in a 24 hour period, or use the maximum dosage of this product for more than 2 weeks, except under the advice and supervision of a doctor.

Directions

- chew 2-4 tablets as symptoms occur, or as directed by a doctor

Other information

- do not use if printed seal under the cap is torn or missing

Inactive ingredients

adipic acid, corn starch, crospovidone, d&c red 27 lake, D&C red 30 lake, D&C yellow 10 lake, dextrose, FD&C yellow 6 lake, flavors, magnesium stearate, maltodextrin, sucrose, talc

PDP

Compare to the active ingredient in TUMS EX

Extra strength

Alkums Antacid Tablets

Assorted Fruit Flavors

Calcium carbonate 750 mg

Relieves:

Acid indigestion

Heartburn